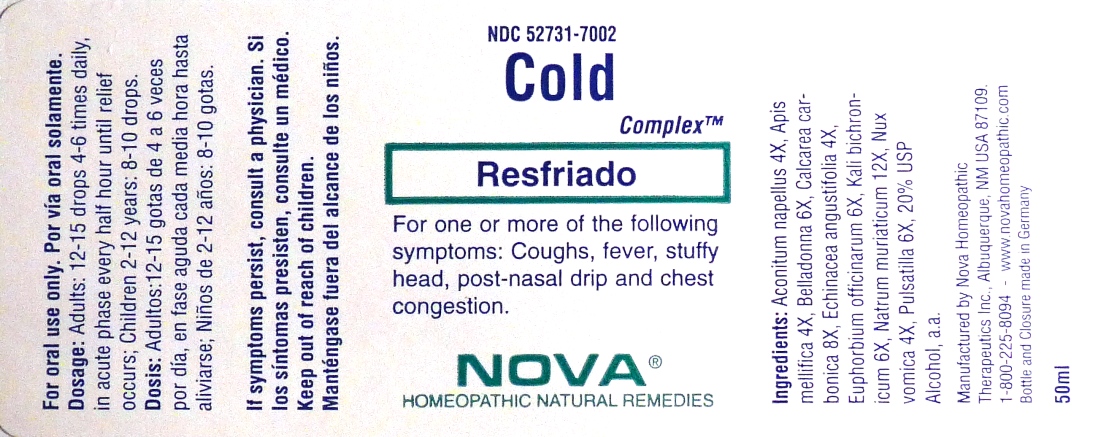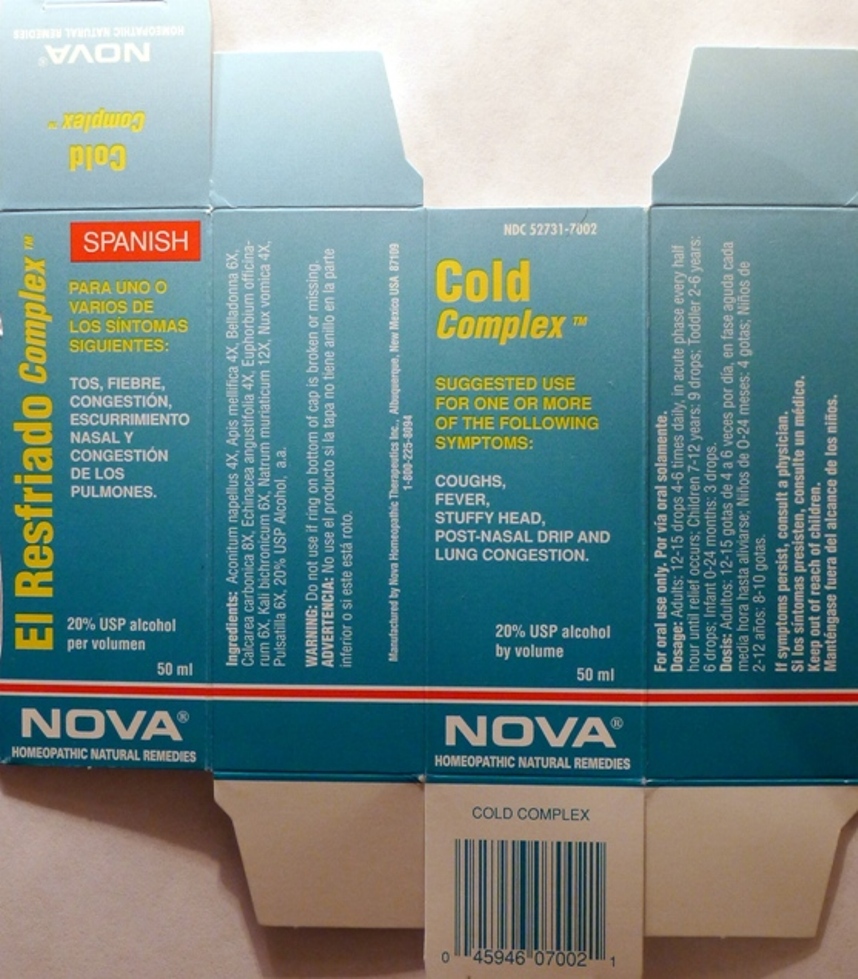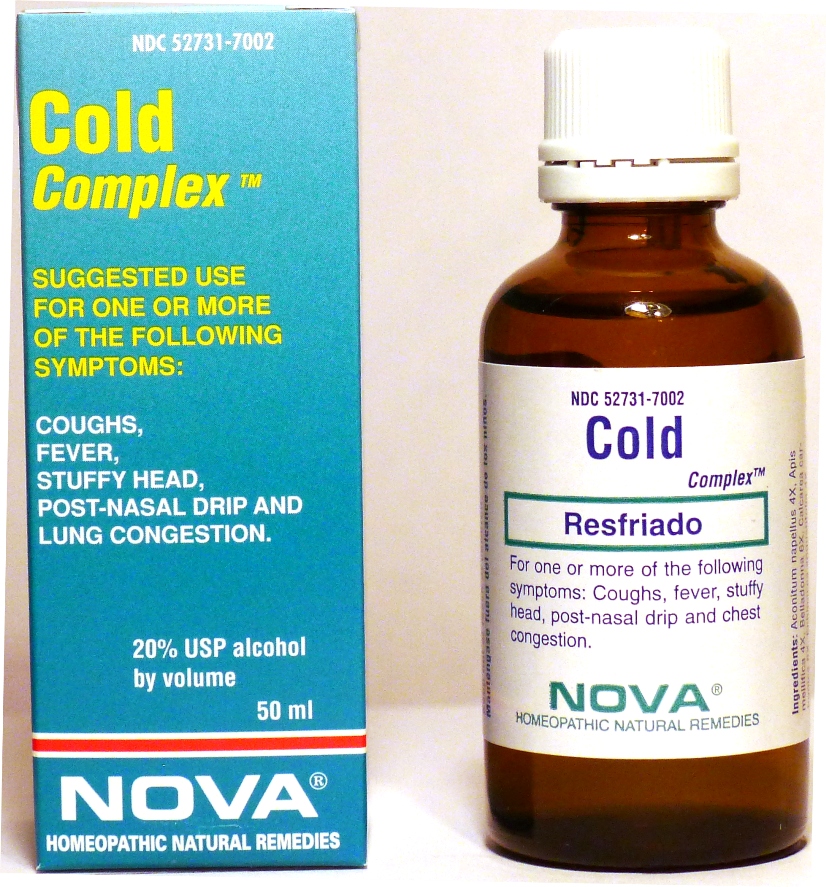 DRUG LABEL: Cold Complex
NDC: 52731-7002 | Form: LIQUID
Manufacturer: Nova Homeopathic Therapeutics, Inc.
Category: homeopathic | Type: HUMAN OTC DRUG LABEL
Date: 20110601

ACTIVE INGREDIENTS: ACONITUM NAPELLUS 4 [hp_X]/1 mL; APIS MELLIFERA 4 [hp_X]/1 mL; ATROPA BELLADONNA 6 [hp_X]/1 mL; OYSTER SHELL CALCIUM CARBONATE, CRUDE 8 [hp_X]/1 mL; ECHINACEA ANGUSTIFOLIA 4 [hp_X]/1 mL; EUPHORBIA RESINIFERA RESIN 6 [hp_X]/1 mL; POTASSIUM DICHROMATE 6 [hp_X]/1 mL; SODIUM CHLORIDE 12 [hp_X]/1 mL; STRYCHNOS NUX-VOMICA SEED 4 [hp_X]/1 mL; PULSATILLA VULGARIS 6 [hp_X]/1 mL
INACTIVE INGREDIENTS: ALCOHOL

Cold Complex

Purpose:

Suggested use for one or more of the following symptoms:

Coughs, fever, stuffy head, post-nasal drip and chest congestion.

Usage and Dosage:

For oral use only.

DOSAGE AND ADMINISTRATION

Adults:

In Accute Phase:
12-15 drops, every half hour until relief occurs
When Relief Occurs:
12-15 drops, 4-6 times daily
Children 2-12 years:
8-10 drops, 4-6 times daily

Warnings:

Keep out of reach of children.

WARNINGS

If symptoms persist, consult a physician.

Do not use if ring on bottom of cap is broken or missing.

Active Ingredients:

Aconitum napellus 4X, Apis mellifica 4X, Belladonna 6X, Calcarea carbonica 8X, Echinacea angustifolia 4X, Euphorbium officinarum 6X, Kali bichronicum 6X, Natrum muriaticum 12X, Nux vomica 4X, Pulsatilla 6X

Inactive Ingredients:

Alcohol, 20% USP

QUESTIONS

Manufactured by Nova Homeopathic Therapeutics Inc., Albuquerque, New Mexico USA 87109

1-800-225-8094

PACKAGE LABEL

Cold Complex Product

Cold Complex Bottle Label

Cold Complex Box